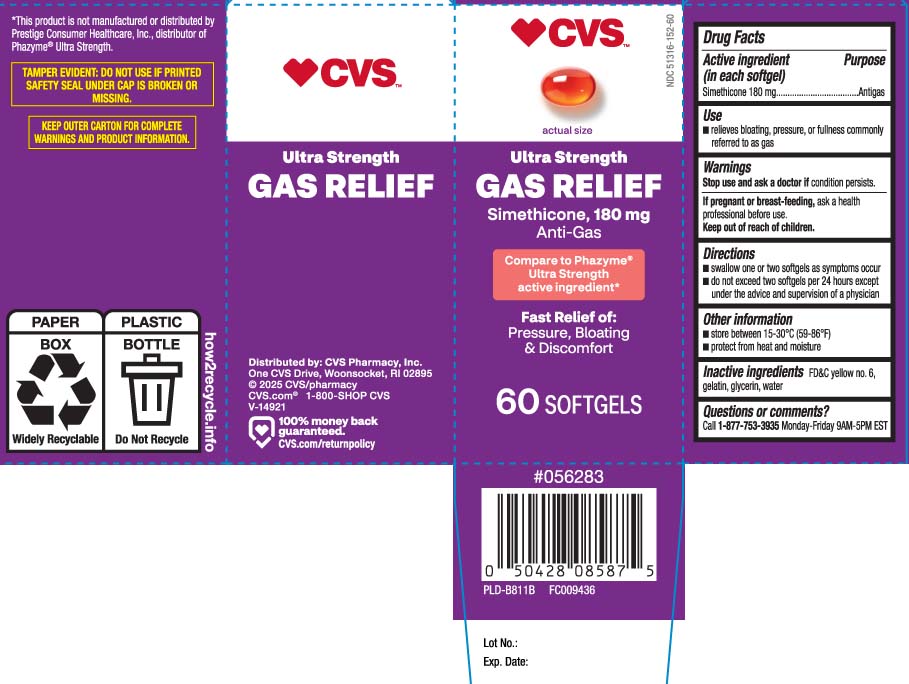 DRUG LABEL: Gas Relief
NDC: 51316-152 | Form: CAPSULE, LIQUID FILLED
Manufacturer: CVS PHARMACY, INC
Category: otc | Type: HUMAN OTC DRUG LABEL
Date: 20251020

ACTIVE INGREDIENTS: DIMETHICONE 180 mg/1 1
INACTIVE INGREDIENTS: FD&C YELLOW NO. 6; GELATIN; GLYCERIN; WATER

Drug Facts

Active ingredient (in each softgel)

Simethicone 180 mg

Purpose

Antigas

Use

- relieves bloating, pressure, or fullness commonly referred to as gas

Warnings

Stop use and ask a doctor if

condition persists.

If pregnant or breast-feeding,

ask a health professional before use.

Directions

- swallow one or two softgels as symptoms occur
- do not exceed two softgels per 24 hours except under the advice and supervision of a physician

Other information

- store between 15-30ºC (59-86ºF)
- protect from heat and moisture

Inactive ingredients

FD&C yellow #6, gelatin, glycerin, water

Questions or comments?

Call 1-877-753-3935 Monday-Friday 9AM-5PM EST

Principal Display Panel

Compare to Phazyme® Ultra Strength active ingredient*

Ultra Strength

GAS RELIEF

Simethicone, 180 mg

Anti-gas

Fast Relief of: Pressure, Bloating, & Discomfort

SOFTGELS

*This product is not manufactured or distributed by Prestige Consumer Healthcare, Inc., distributor of Phazyme® Ultra Strength.

TAMPER EVIDENT: DO NOT USE IF BLISTER UNIT IS TORN, BROKEN OR SHOWS ANY SIGNS OF TAMPERING.

KEEP OUTER CARTON FOR COMPLETE WARNINGS AND PRODUCT INFORMATION.

Distributed by:

CVS Pharmacy, Inc.

One CVS Drive

Woonsocket, RI 02895

Package Label

CVS Ultra Strength Gas Relief